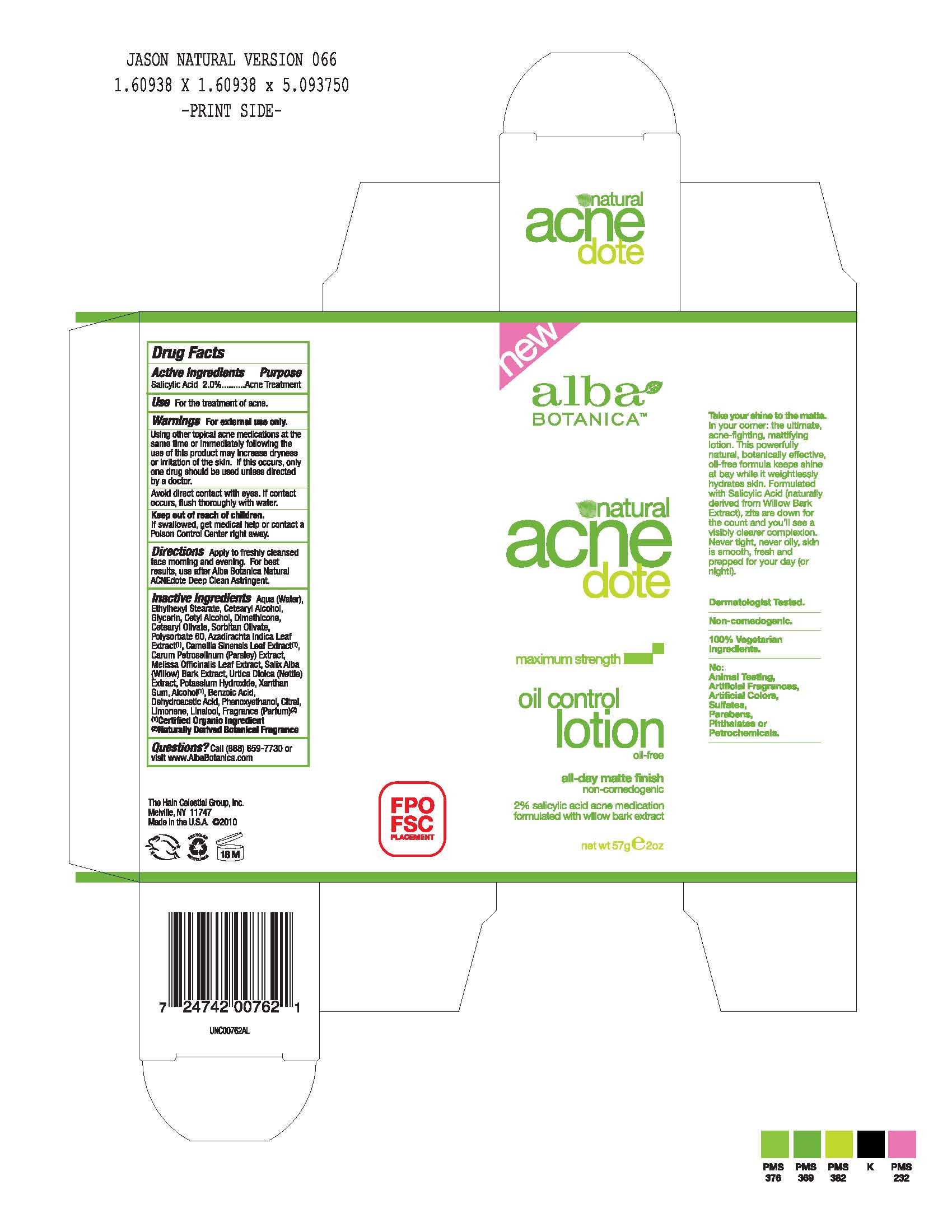 DRUG LABEL: Alba Natural Acnedote 
NDC: 61995-2762 | Form: LOTION
Manufacturer: The Hain Celestial Group, Inc.
Category: otc | Type: HUMAN OTC DRUG LABEL
Date: 20100721

ACTIVE INGREDIENTS: Salicylic Acid 2.0 g/100 g

Drug Facts

ACTIVE INGREDIENTS

Salicylic Acid 2.0%

USE

- For the treatment of acne
- Apply to freshly cleansed face morning and evening
- For the best results, use after Alba Botanica Natural ACNEdote Deep Clean Astringent

WARNINGS

For external use only. Using other topical acne medications at the same time or immediately following the use of this product may increase dryness or irritation of the skin. If this occurs,only one drug should be used unless directed by a doctor.

Avoid direct contact with eyes. If contact occurs, flush thoroughly with water.

Keep out of reach of children. If swallowed, get medical help or contact a Poison Control Center right away.

QUESTIONS?

Call (888) 659-7730 or visit www.AlbaBotanica.com

The Hain Celestial Group, Inc.

Melville, NY 11747

Made in U.S.A.